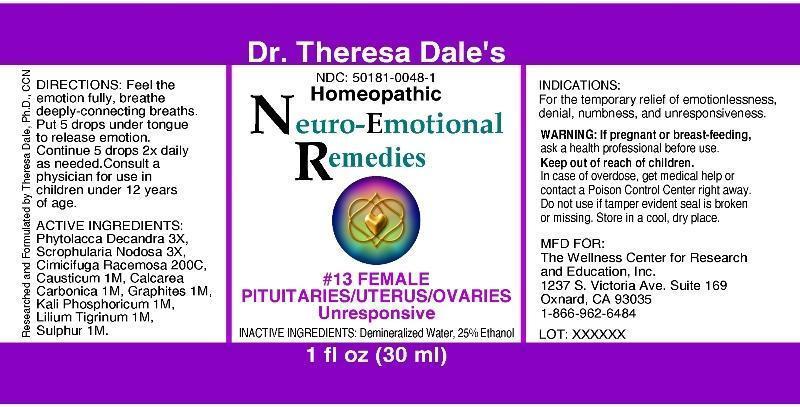 DRUG LABEL: 13 Female
NDC: 50181-0048 | Form: LIQUID
Manufacturer: The Wellness Center For Research and Education
Category: homeopathic | Type: HUMAN OTC DRUG LABEL
Date: 20250530

ACTIVE INGREDIENTS: PHYTOLACCA AMERICANA ROOT 3 [hp_X]/1 mL; SCROPHULARIA NODOSA 3 [hp_X]/1 mL; BLACK COHOSH 200 [hp_C]/1 mL; OYSTER SHELL CALCIUM CARBONATE, CRUDE 1 [hp_M]/1 mL; CAUSTICUM 1 [hp_M]/1 mL; GRAPHITE 1 [hp_M]/1 mL; POTASSIUM PHOSPHATE, DIBASIC 1 [hp_M]/1 mL; LILIUM LANCIFOLIUM WHOLE FLOWERING 1 [hp_M]/1 mL; SULFUR 1 [hp_M]/1 mL
INACTIVE INGREDIENTS: WATER; ALCOHOL

DRUG FACTS:

ACTIVE INGREDIENT:

Phytolacca Decandra 3X, Scrophularia Nodosa 3X, Cimicifuga Racemosa 200C, Calcarea Carbonica 1M, Causticum 1M, Graphites 1M, Kali Phosphoricum 1M, Lilium Tigrinum 1M, Sulphur 1M

INDICATIONS:

For the temporary relief of emotionlessness, denial, numbness, and unresponsiveness.

WARNINGS:

If pregnant or breast-feeding, ask a health care professional before use.

Keep out of reach of children. In case of overdose, get medical help or contact a Poison Control Center right away.

Do not use if tamper evident seal is broken or missing.

Store in cool, dry place.

Keep out of reach of children. In case of overdose, get medical help or contact a Poison Control Center right away.

DIRECTIONS:

Feel the emotion fully, breathe deeply-connecting breaths. Put 5 drops under tongue to release emotion. Continue 5 drops 2x daily as needed. Consult a physician for use in children under 12 years of age.

INDICATIONS:

For the temporary relief of emotionlessness, denial, numbness, and unresponsiveness.

INACTIVE INGREDIENTS:

Demineralized Water, 25% Ethanol.

QUESTIONS:

MFD FOR:

The Wellness Center for Research and Education, Inc.

1237 S. Victoria Ave. Suite 169

Oxnard, CA 93035

1-866-962-6484

PACKAGE LABEL DISPLAY

Dr. Theresa Dale's

NDC: 50181-0048-1

Homeopathic

Neuro-Emotional Remedies

#13 FEMALE

PITUITARIES/UTERUS/OVARIES

UNRESPONSIVE

1 fl oz (30 ml)